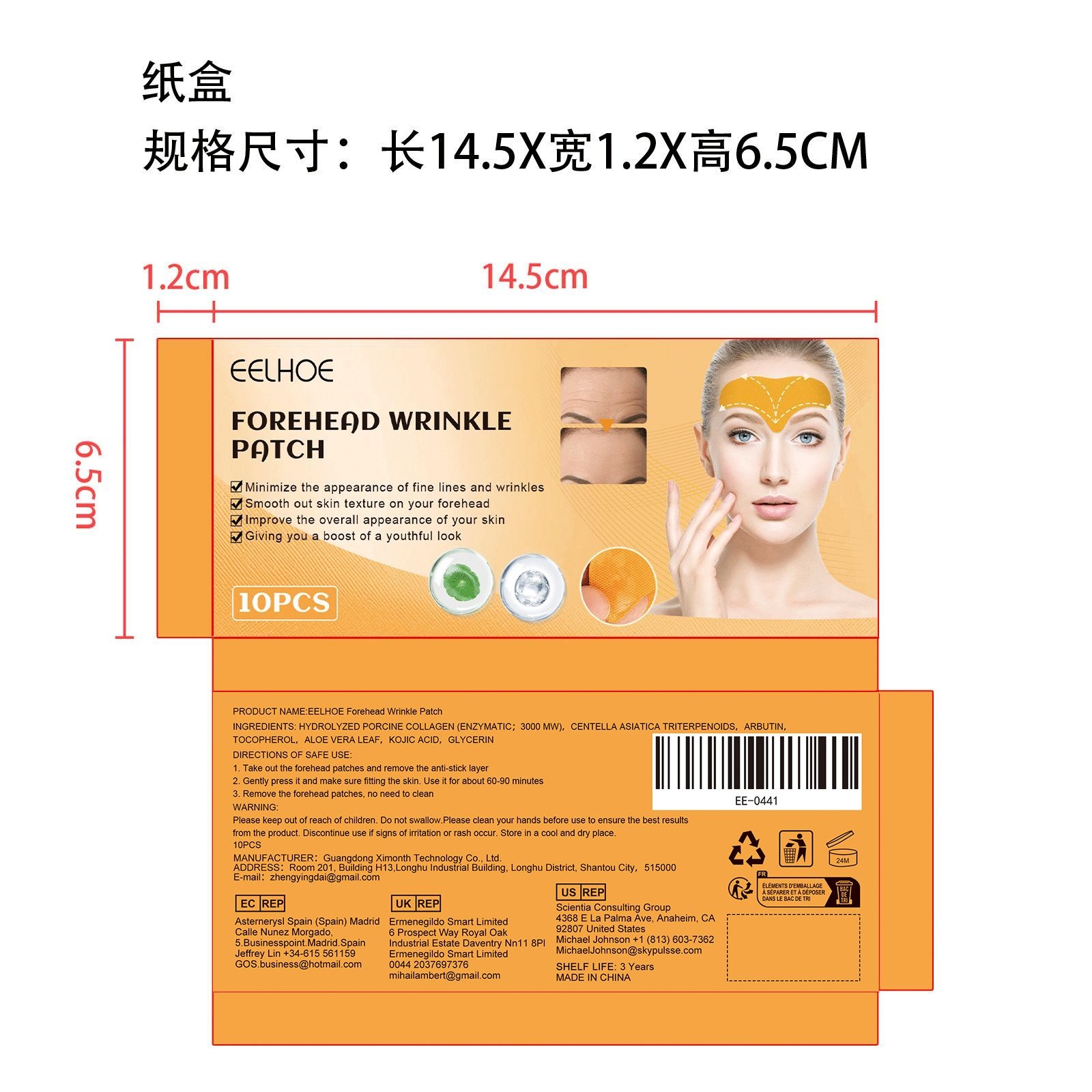 DRUG LABEL: EELHOE Forehead Wrinkle Patch
NDC: 84660-040 | Form: PATCH
Manufacturer: Guangdong Ximonth Technology Co., Ltd.
Category: otc | Type: HUMAN OTC DRUG LABEL
Date: 20241008

ACTIVE INGREDIENTS: HYDROLYZED PORCINE COLLAGEN (ENZYMATIC; 3000 MW) 1 mg/10 mg; KOJIC ACID 1 mg/10 mg; ARBUTIN 1 mg/10 mg; ALOE VERA LEAF 1 mg/10 mg; TOCOPHEROL 1 mg/10 mg; CENTELLA ASIATICA TRITERPENOIDS 1 mg/10 mg
INACTIVE INGREDIENTS: GLYCERIN 4 mg/10 mg

Active Ingredient(s)

HYDROLYZED PORCINE COLLAGEN (ENZYMATIC；3000 MW)，CENTELLA ASIATICA TRITERPENOIDS，ARBUTIN，TOCOPHEROL，ALOE VERA LEAF，KOJIC ACID

Purpose

Minimize the appearance of fine lines and wrinkles

Use

1. Take out the forehead patches and remove the anti-stick layer
2. Gently press it and make sure fitting the skin. Use it for about 60-90 minutes
3. Remove the forehead patches, no need to clean

STOP USE

Discontinue use if signs of irritation or rash occur.

Do not use

Discontinue use if signs of irritation or rash occur.

Warnings

Please keep out of reach of children.Do not swallow.Please clean your hands before use to ensure the best results from the product.Discontinue use if signs of irritation or rash occur.Store in a cool and dry place.

KEEP OUT OF REACH OF CHILDREN

Please keep out of reach of children. Do not swallow.

STORAGE AND HANDLING

Avoid freezing and excessive heat above 40C (104F) ）
Store in a cool and dry place.

INACTIVE INGREDIENT

GLYCERIN